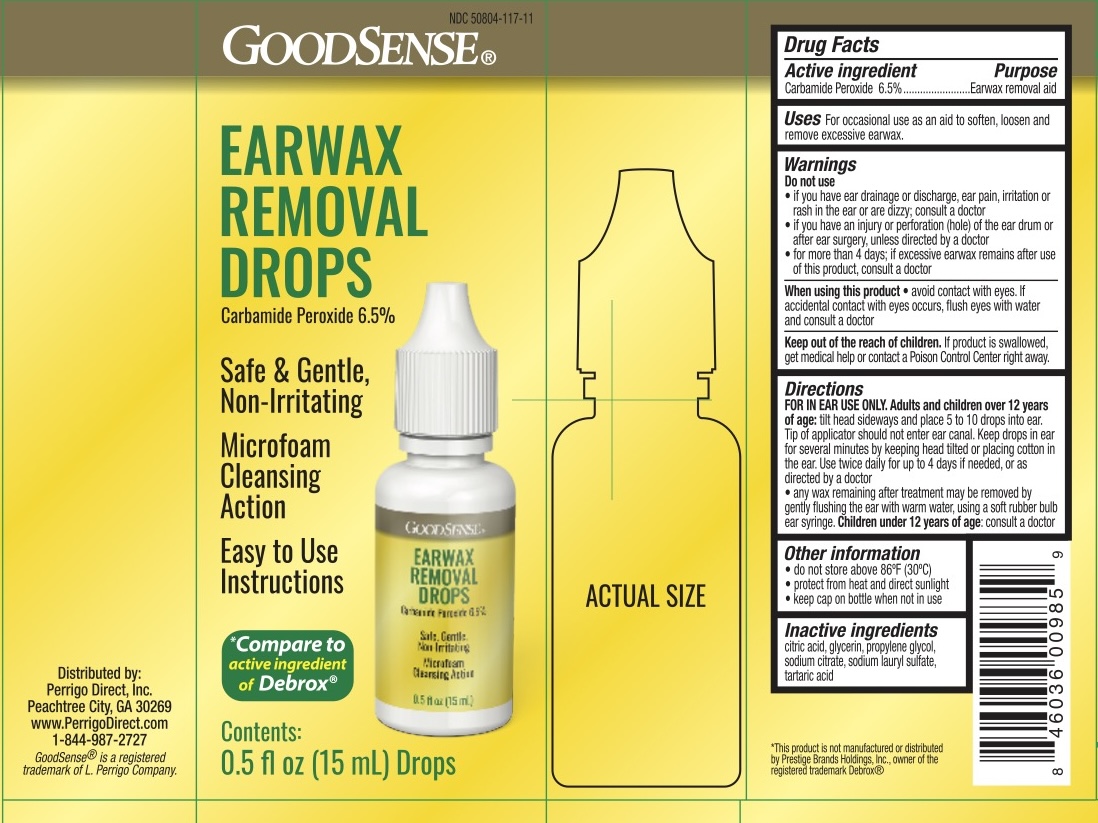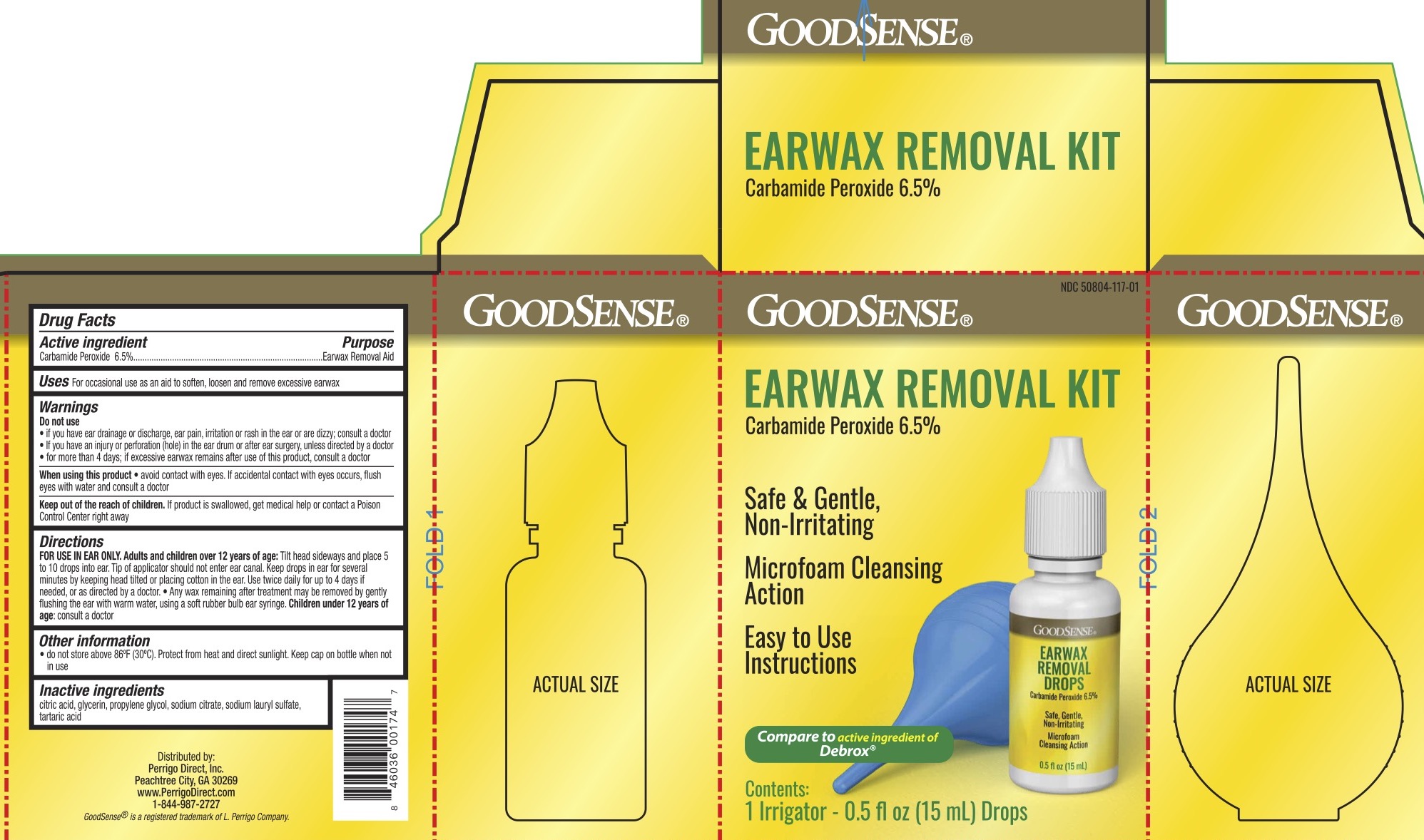 DRUG LABEL: GoodSense Ear Wax Removal Kit
NDC: 50804-117 | Form: LIQUID
Manufacturer: Geiss, Destin & Dunn, Inc
Category: otc | Type: HUMAN OTC DRUG LABEL
Date: 20250919

ACTIVE INGREDIENTS: CARBAMIDE PEROXIDE 6.5 g/100 mL
INACTIVE INGREDIENTS: PROPYLENE GLYCOL; GLYCERIN; SODIUM CITRATE; SODIUM LAURYL SULFATE; TARTARIC ACID; CITRIC ACID

GoodSense Ear Wax

ACTIVE INGREDIENT

Carbamide Peroxide 6.5%

PURPOSE

Earwax removal aid

INDICATIONS AND USAGE

For occasional use as an aid to soften, loosen, and remove excessive earwax.

Do not use

- if you have ear drainage or discharge, ear pain, irritation or rash in the ear or are dizzy; consult a doctor
- if you have an injury or perforation (hole) in the ear drum or after ear surgery, unless directed by a doctor
- for more than 4 days; if excessive earwax remains after use of this product, consult a doctor

When using this product avoid contact with yes. If accidental contact with yes occurs, flush eyes with water and consult a doctor.

Keep out of reach of children. If the product is swallowed, get medical help or contact a Poison Control Center right away.

DOSAGE AND ADMINISTRATION

FOR USE IN EAR ONLY. Adults and children over 12 years of age: tilt head sideways and place 5 to 10 drops into ear. Tip of applicator should not enter ear canal. Keep drops in ear for several minutes by keeping head tilted or placing cotton in the ear. Use twice daily for up to 4 days if needed, or as directed by a doctor. Any wax remaining after treatment may be removed by gently flushing the ear with warm water, using a soft rubber bulb ear syringe. Children under 12 years of age: consult a doctor.

INACTIVE INGREDIENT

Citric acid, glycerin, propylene glycol, sodium citrate, sodium lauryl sulfate, tartaric acid